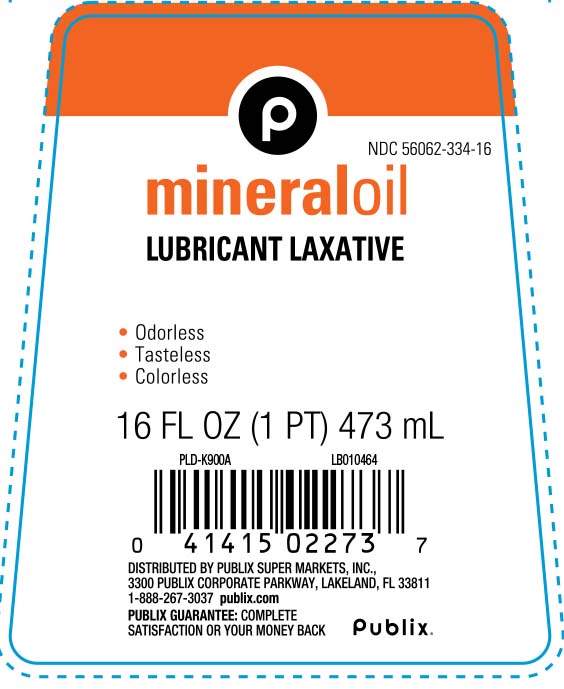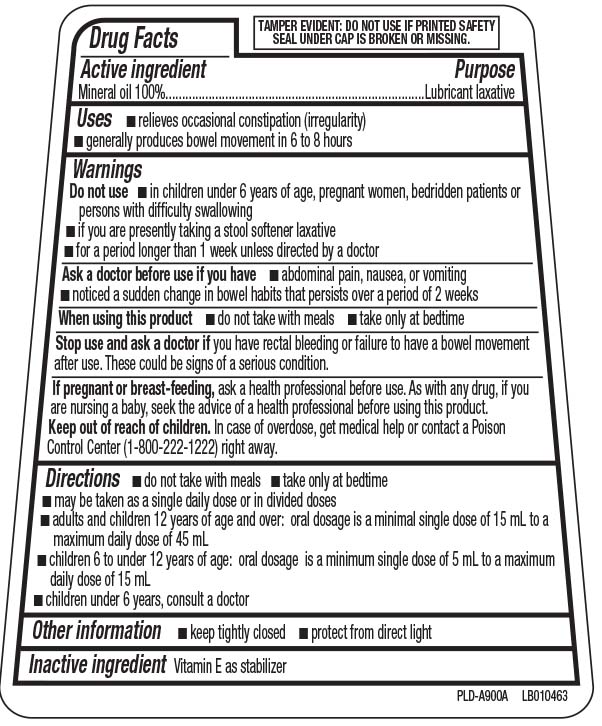 DRUG LABEL: Mineral Oil
NDC: 56062-334 | Form: OIL
Manufacturer: Publix Supermarkets, Inc.
Category: otc | Type: HUMAN OTC DRUG LABEL
Date: 20250530

ACTIVE INGREDIENTS: MINERAL OIL 100 mg/100 mL
INACTIVE INGREDIENTS: TOCOPHEROL

Drug Facts

Active Ingredient

Mineral Oil 100%

Purpose

Lubricant laxative

Uses

- relieves occasional constipation (irregularity)
- generally produces bowel movement in 6 to 8 hours

Warnings

Do not use

- in children under 6 years of age, pregnant wormen, bedridden patients or persons with difficulty swallowing
- if you are presently taking a stool softener laxative
- for longer than 1 week unless directed by a doctor

Ask a doctor before use if you have

- abdominal pain, nausea or vomiting
- noticed a sudden change in bowel habits that persists over a period of 2 weeks

When using this product

- do not take with meals
- take only at bedtime

Stop use and ask a doctor if you have

rectal bleeding or failure to have a bowel movement after use. These could be signs of a serious condition.

If pregnant or breast feeding,

ask a health professional before use. As with any drug, if you are nursing a baby, seek the advice of a health professional before using this product.

Keep out of reach of children

In case of overdose, get medical help or contact a Poison Control center (1-800-222-1222) right away.

Directions

- do not take with meals
- take only at bedtime
- may be taken as a single daily dose or in divided doses
- adults and children 12 years of age and over
  - 1 to 3 tablespoons (15 to 45 mL)
  - maximum 3 tablespoons (45 mL) in 24 hours
- children under 12 years, consult a doctor

Other Information

- keep tightly closed
- protect from direct light

Inactive Ingredient

Vitamin E as stabilizer

Principal Display Panel

Mineral oil

LUBRICANT LAXATIVE

- odorless
- tasteless
- colorless

FL OZ (mL)

TAMPER EVIDENT: DO NOT USE IF PRINTED SAFETY SEAL UNDER CAP IS BROKEN OR MISSING.

DISTRIBUTED BY PUBLIX SUPER MARKETS, INC.,

3300 PUBLIX CORPORATE PARKWAY

LAKELAND, FL 33811

publix.com

Package Label

Mineral Oil Lubricant Laxative front label
Mineral Oil Lubricant Laxative back label